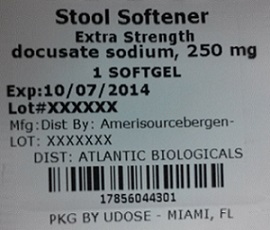 DRUG LABEL: STOOL SOFTENER
                                    
NDC: 17856-0443 | Form: CAPSULE, LIQUID FILLED
Manufacturer: Atlantic Biologicals Corps
Category: otc | Type: HUMAN OTC DRUG LABEL
Date: 20121109

ACTIVE INGREDIENTS: DOCUSATE SODIUM 250 mg/1 1
INACTIVE INGREDIENTS: FD&C RED NO. 40; FD&C YELLOW NO. 6; GELATIN; GLYCERIN; POLYETHYLENE GLYCOLS; PROPYLENE GLYCOL; WATER; SORBITOL

Drug Facts

Active ingredient (in each softgel)

Docusate Sodium 250 mg

Purpose

Stool softener

Uses

- for the prevention of dry, hard stools
- for relief of occasional constipation.
- this product generally produces a bowel movement within 12 to 72 hours.

Warnings - Do not use

- if you are currently taking mineral oil, unless directed by a doctor
- when abdominal pain, nausea, or vomiting are present
- for more than 1 week, unless directed by a doctor

Ask a doctor before use if

you notice a sudden change in bowel habits that persists over a period of 2 weeks

Stop use and ask a doctor if

- you have rectal bleeding
- you fail to have a bowel movement after use

If pregnant or breast-feeding,

ask a health professional before use.

Keep out of reach of children.

In case of overdose, get medical help or contact a Poison Control Center right away.

Directions

- take 1 softgel daily or as directed by a doctor adults and children over 12 years of age and over:
- : take as directed by a doctor children under 12 years of age

Other information

- sodium 15 mg each softgel contains:
- store at controlled room temperature 15 - 30 C (59 - 86 F)oooo
- do not use if imprinted safety seal under cap is broken or missing

Inactive Ingredients

edible white ink, FD&C Red No# 40, FD&C Yellow No# 6, gelatin, glycerin, polyethylene glycol, propylene glycol, purified water and sorbitol special.

Questions or comments?

Call toll free 1-877-753-3935